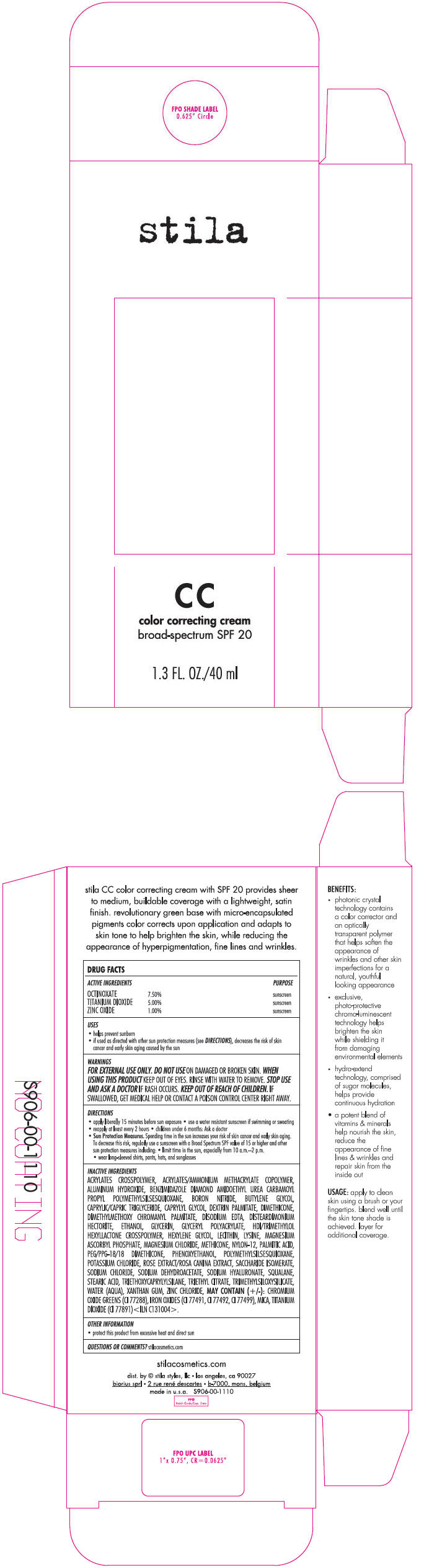 DRUG LABEL: Stila Color Correcting Broad Spectrum SPF 20 
NDC: 76049-906 | Form: CREAM
Manufacturer: Stila Styles, LLC
Category: otc | Type: HUMAN OTC DRUG LABEL
Date: 20131122

ACTIVE INGREDIENTS: OCTINOXATE 75 mg/1 mL; TITANIUM DIOXIDE 50 mg/1 mL; ZINC OXIDE 10 mg/1 mL
INACTIVE INGREDIENTS: ALUMINUM HYDROXIDE; BORON NITRIDE; BUTYLENE GLYCOL; MEDIUM-CHAIN TRIGLYCERIDES; CAPRYLYL GLYCOL; DIMETHICONE; DIMETHYLMETHOXY CHROMANYL PALMITATE; EDETATE DISODIUM; DISTEARDIMONIUM HECTORITE; ALCOHOL; GLYCERIN; HEXYLENE GLYCOL; LYSINE; MAGNESIUM ASCORBYL PHOSPHATE; MAGNESIUM CHLORIDE; NYLON-12; PALMITIC ACID; PEG/PPG-18/18 DIMETHICONE; PHENOXYETHANOL; POTASSIUM CHLORIDE; SACCHARIDE ISOMERATE; SODIUM CHLORIDE; SODIUM DEHYDROACETATE; HYALURONATE SODIUM; SQUALANE; STEARIC ACID; TRIETHOXYCAPRYLYLSILANE; TRIETHYL CITRATE; WATER; XANTHAN GUM; ZINC CHLORIDE; CHROMIC OXIDE; FERRIC OXIDE RED; FERRIC OXIDE YELLOW; FERROSOFERRIC OXIDE; MICA

Stila Color Correcting Broad Spectrum SPF 20
(All Shades)

DRUG FACTS

ACTIVE INGREDIENT

ACTIVE INGREDIENTS |  | PURPOSE
OCTINOXATE | 7.50% | sunscreen
TITANIUM DIOXIDE | 5.00% | sunscreen
ZINC OXIDE | 1.00% | sunscreen

USES

- helps prevent sunburn
- if used as directed with other sun protection measures (see DIRECTIONS), decreases the risk of skin cancer and early skin aging caused by the sun

WARNINGS

FOR EXTERNAL USE ONLY.

DO NOT USE ON DAMAGED OR BROKEN SKIN.

WHEN USING THIS PRODUCT KEEP OUT OF EYES. RINSE WITH WATER TO REMOVE.

STOP USE AND ASK A DOCTOR IF RASH OCCURS.

KEEP OUT OF REACH OF CHILDREN. IF SWALLOWED, GET MEDICAL HELP OR CONTACT A POISON CONTROL CENTER RIGHT AWAY.

DIRECTIONS

- apply liberally 15 minutes before sun exposure
- use a water resistant sunscreen if swimming or sweating
- reapply at least every 2 hours
- children under 6 months: Ask a doctor
- Sun Protection Measures. Spending time in the sun increases your risk of skin cancer and early skin aging. To decrease this risk, regularly use a sunscreen with a Broad Spectrum SPF value of 15 or higher and other sun protection measures including:
  - limit time in the sun, especially from 10 a.m.–2 p.m.
  - wear long-sleeved shirts, pants, hats, and sunglasses

INACTIVE INGREDIENTS

ACRYLATES CROSSPOLYMER, ACRYLATES/AMMONIUM METHACRYLATE COPOLYMER, ALUMINUM HYDROXIDE, BENZIMIDAZOLE DIAMOND AMIDOETHYL UREA CARBAMOYL PROPYL POLYMETHYLSILSESQUIOXANE, BORON NITRIDE, BUTYLENE GLYCOL, CAPRYLIC/CAPRIC TRIGLYCERIDE, CAPRYLYL GLYCOL, DEXTRIN PALMITATE, DIMETHICONE, DIMETHYLMETHOXY CHROMANYL PALMITATE, DISODIUM EDTA, DISTEARDIMONIUM HECTORITE, ETHANOL, GLYCERIN, GLYCERYL POLYACRYLATE, HDI/TRIMETHYLOL HEXYLLACTONE CROSSPOLYMER, HEXYLENE GLYCOL, LECITHIN, LYSINE, MAGNESIUM ASCORBYL PHOSPHATE, MAGNESIUM CHLORIDE, METHICONE, NYLON-12, PALMITIC ACID, PEG/PPG-18/18 DIMETHICONE, PHENOXYETHANOL, POLYMETHYLSILSESQUIOXANE, POTASSIUM CHLORIDE, ROSE EXTRACT/ROSA CANINA EXTRACT, SACCHARIDE ISOMERATE, SODIUM CHLORIDE, SODIUM DEHYDROACETATE, SODIUM HYALURONATE, SQUALANE, STEARIC ACID, TRIETHOXYCAPRYLYLSILANE, TRIETHYL CITRATE, TRIMETHYLSILOXYSILICATE, WATER (AQUA), XANTHAN GUM, ZINC CHLORIDE, MAY CONTAIN (+/-): CHROMIUM OXIDE GREENS (CI 77288), IRON OXIDES (CI 77491, CI 77492, CI 77499), MICA, TITANIUM DIOXIDE (CI 77891) <ILN C131004>.

OTHER INFORMATION

- protect this product from excessive heat and direct sun

QUESTIONS OR COMMENTS?

stilacosmetics.com

dist. by © stila styles, llc • los angeles, ca 90027

PRINCIPAL DISPLAY PANEL - 40 ml Tube Carton

stila

CC

color correcting cream
broad-spectrum SPF 20

1.3 FL. OZ./40 ml